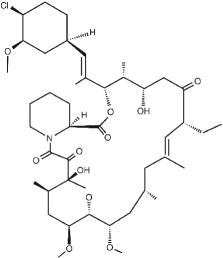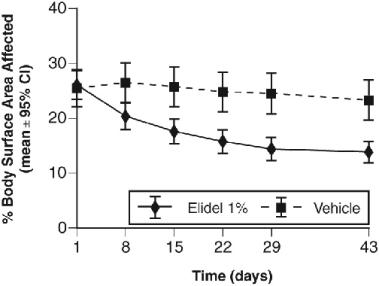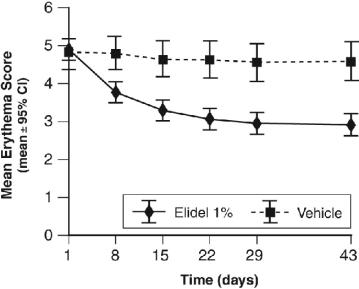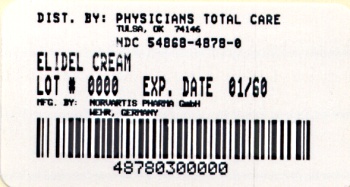 DRUG LABEL: Elidel
NDC: 54868-4878 | Form: CREAM
Manufacturer: Physicians Total Care, Inc.
Category: prescription | Type: HUMAN PRESCRIPTION DRUG LABEL
Date: 20090809

ACTIVE INGREDIENTS: PIMECROLIMUS 10 mg/1 g
INACTIVE INGREDIENTS: BENZYL ALCOHOL; CETYL ALCOHOL; CITRIC ACID MONOHYDRATE; GLYCERYL MONOSTEARATE; OLEYL ALCOHOL; PROPYLENE GLYCOL; SODIUM CETOSTEARYL SULFATE; SODIUM HYDROXIDE; STEARYL ALCOHOL; WATER

Elidel

Elidel®

(pimecrolimus) Cream 1%

FOR DERMATOLOGIC USE ONLY

NOT FOR OPHTHALMIC USE

Rx only

Prescribing Information

See WARNINGS, boxed WARNING concerning long-term safety of topical calcineurin inhibitors.

DESCRIPTION

ELIDEL ® (pimecrolimus) Cream 1% contains the compound pimecrolimus, the immunosuppressant 33-epi-chloro-derivative of the macrolactam ascomycin.

Chemically, pimecrolimus is (1R,9S,12S,13R,14S,17R,18E,21S,23S,24R,25S,27R)-12-[(1E)-2-{(1R,3R,4S)-4-chloro-3-methoxycyclohexyl}-1-methylvinyl]-17-ethyl-1,14-dihydroxy-23,25-dimethoxy-13,19,21,27-tetramethyl-11,28-dioxa-4-aza-tricyclo[22.3.1.0 ^4,9]octacos-18-ene-2,3,10,16-tetraone.

The compound has the empirical formula C 43H68CINO11 and the molecular weight of 810.47. The structural formula is

Pimecrolimus is a white to off-white fine crystalline powder. It is soluble in methanol and ethanol and insoluble in water.

Each gram of ELIDEL Cream 1% contains 10 mg of pimecrolimus in a whitish cream base of benzyl alcohol, cetyl alcohol, citric acid, mono- and di-glycerides, oleyl alcohol, propylene glycol, sodium cetostearyl sulphate, sodium hydroxide, stearyl alcohol, triglycerides, and water.

CLINICAL PHARMACOLOGY

Mechanism of Action/Pharmacodynamics

The mechanism of action of pimecrolimus in atopic dermatitis is not known. While the following have been observed, the clinical significance of these observations in atopic dermatitis is not known. It has been demonstrated that pimecrolimus binds with high affinity to macrophilin-12 (FKBP-12) and inhibits the calcium-dependent phosphatase, calcineurin. As a consequence, it inhibits T cell activation by blocking the transcription of early cytokines. In particular, pimecrolimus inhibits at nanomolar concentrations Interleukin-2 and interferon gamma (Th1-type) and Interleukin-4 and Interleukin-10 (Th2-type) cytokine synthesis in human T cells. In addition, pimecrolimus prevents the release of inflammatory cytokines and mediators from mast cells in vitro after stimulation by antigen/IgE.

Pharmacokinetics

Absorption

In adult patients (n=52) being treated for atopic dermatitis [13%-62% Body Surface Area (BSA) involvement] for periods up to a year, a maximum pimecrolimus concentration of 1.4 ng/mL was observed among those subjects with detectable blood levels. In the majority of samples in adult (91%; 1,244/1,362) subjects, blood concentrations of pimecrolimus were below 0.5 ng/mL. Data on blood levels of pimecrolimus measured in pediatric patients are described below in Special Populations, Pediatrics.

Distribution

Laboratory in vitro plasma protein binding studies using equilibrium gel filtration have shown that 99.5% of pimecrolimus in plasma is bound to proteins over the pimecrolimus concentration range of 2-100 ng/mL tested. The major fraction of pimecrolimus in plasma appears to be bound to various lipoproteins. As with other topical calcineurin inhibitors, it is not known whether pimecrolimus is absorbed into cutaneous lymphatic vessels or in regional lymph nodes.

Metabolism

Following the administration of a single oral radiolabeled dose of pimecrolimus numerous circulating O-demethylation metabolites were seen. Studies with human liver microsomes indicate that pimecrolimus is metabolized in vitro by the CYP3A sub-family of metabolizing enzymes. No evidence of skin mediated drug metabolism was identified in vivo using the minipig or in vitro using stripped human skin.

Elimination

Based on the results of the aforementioned radiolabeled study, following a single oral dose of pimecrolimus ~81% of the administered radioactivity was recovered, primarily in the feces (78.4%) as metabolites. Less than 1% of the radioactivity found in the feces was due to unchanged pimecrolimus.

Special Populations

Pediatrics

The systemic exposure to pimecrolimus from ELIDEL ® (pimecrolimus) Cream 1% was investigated in 28 pediatric patients with atopic dermatitis (20%-80% BSA involvement) between the ages of 8 months-14 yrs. Following twice daily application for three weeks, blood concentrations of pimecrolimus were <2 ng/mL with 60% (96/161) of the blood samples having blood concentration below the limit of quantification (0.5 ng/mL). However, the children (23 children out of the total 28 children investigated) had at least one detectable blood level as compared to the adults (12 adults out of the total 52 adults investigated) over a 3-week treatment period. Due to the erratic nature of the blood levels observed, no correlation could be made between amount of cream, degree of BSA involvement, and blood concentrations. In general, the blood concentrations measured in adult atopic dermatitis patients were comparable to those seen in the pediatric population.

In a second group of 30 pediatric patients aged 3-23 months with 10%-92% BSA involvement, following twice daily application for three weeks, blood concentrations of pimecrolimus were <2.6 ng/mL with 65% (75/116) of the blood samples having blood concentration below 0.5ng/mL, and 27% (31/116) below the limit of quantification (0.1 ng/mL) for these studies.

Overall, a higher proportion of detectable blood levels was seen in the pediatric patient population as compared to adult population. This increase in the absolute number of positive blood levels may be due to the larger surface area to body mass ratio seen in these younger subjects. In addition, a higher incidence of upper respiratory symptoms/infections was also seen relative to the older age group in the PK studies. At this time, a causal relationship between these findings and ELIDEL use cannot be ruled out.

ELIDEL Cream is not indicated for use in children less than 2 years of age (see INDICATIONS AND USAGE, WARNINGS, boxed WARNING, and PRECAUTIONS, Pediatric Use).

Renal Insufficiency

The effect of renal insufficiency on the pharmacokinetics of topically administered pimecrolimus has not been evaluated but dose-adjustment is not expected to be needed as 80% of the drug is excreted in the feces.

Hepatic Insufficiency

The effect of hepatic insufficiency on the pharmacokinetics of topically administered pimecrolimus has not been evaluated but dose-adjustment is not expected to be needed.

CLINICAL STUDIES

Three randomized, double-blind, vehicle-controlled, multi-center, Phase 3 studies were conducted in 589 pediatric patients ages 3 months-17 years old to evaluate ELIDEL ® (pimecrolimus) Cream 1% for the treatment of mild to moderate atopic dermatitis. Two of the three trials support the use of ELIDEL Cream in patients 2 years and older with mild to moderate atopic dermatitis (see PRECAUTIONS, Pediatric Use). Three other trials in 1,619 pediatric and adult patients provided additional data regarding the safety of ELIDEL Cream in the treatment of atopic dermatitis. Two of these other trials were vehicle-controlled with optional sequential use of a medium potency topical corticosteroid in pediatric patients and one trial was an active comparator trial in adult patients with atopic dermatitis (see PRECAUTIONS, Pediatric Use and ADVERSE REACTIONS).

Two identical 6-week, randomized, vehicle-controlled, multi-center, Phase 3 trials were conducted to evaluate ELIDEL Cream for the treatment of mild to moderate atopic dermatitis. A total of 403 pediatric patients 2-17 years old were included in the studies. The male/female ratio was approximately 50% and 29% of the patients were African American. At study entry, 59% of patients had moderate disease and the mean body surface area (BSA) affected was 26%. About 75% of patients had atopic dermatitis affecting the face and/or neck region. In these studies, patients applied either ELIDEL Cream or vehicle cream twice daily to 5% to 96% of their BSA for up to 6 weeks. At endpoint, based on the physician’s global evaluation of clinical response, 35% of patients treated with ELIDEL Cream were clear or almost clear of signs of atopic dermatitis compared to only 18% of vehicle-treated patients. More ELIDEL patients (57%) had mild or no pruritus at 6 weeks compared to vehicle patients (34%). The improvement in pruritus occurred in conjunction with the improvement of the patients’ atopic dermatitis.

In these two 6-week studies of ELIDEL, the combined efficacy results at endpoint are as follows:

 | % Patients
 | Elidel®(N= 267) | Vehicle(N= 136)
Global Assessment
Clear | 28 (10%) | 5 (4%)
Clear or Almost Clear | 93 (35%) | 25 (18%)
Clear to Mild Disease | 180 (67%) | 55 (40%)

In the two pediatric studies that independently support the use of ELIDEL Cream in mild to moderate atopic dermatitis, a significant treatment effect was seen by day 15. Of the key signs of atopic dermatitis, erythema, infiltration/papulation, lichenification, and excoriations, erythema and infiltration/papulation were reduced at day 8 when compared to vehicle.

The following graph depicts the time course of improvement in the percent body surface area affected as a result of treatment with ELIDEL Cream in 2-17 year olds.

The following graph shows the time course of improvement in erythema as a result of treatment with ELIDEL Cream in 2-17 year olds.

INDICATIONS AND USAGE

ELIDEL ® (pimecrolimus) Cream 1% is indicated as second-line therapy for the short-term and non-continuous chronic treatment of mild to moderate atopic dermatitis in non-immunocompromised adults and children 2 years of age and older, who have failed to respond adequately to other topical prescription treatments, or when those treatments are not advisable.

ELIDEL Cream is not indicated for use in children less than 2 years of age (see WARNINGS, boxed WARNING, and PRECAUTIONS, Pediatric Use).

CONTRAINDICATIONS

ELIDEL ® (pimecrolimus) Cream 1% is contraindicated in individuals with a history of hypersensitivity to pimecrolimus or any of the components of the cream.

WARNINGS

WARNING

Long-term Safety of Topical Calcineurin Inhibitors Has Not Been Established

Although a causal relationship has not been established, rare cases of malignancy (e.g., skin and lymphoma) have been reported in patients treated with topical calcineurin inhibitors, including ELIDEL Cream.

Therefore:

- Continuous long-term use of topical calcineurin inhibitors, including ELIDEL Cream, in any age group should be avoided, and application limited to areas of involvement with atopic dermatitis.
- ELIDEL Cream is not indicated for use in children less than 2 years of age.

Prolonged systemic use of calcineurin inhibitors for sustained immunosuppression in animal studies and transplant patients following systemic administration has been associated with an increased risk of infections, lymphomas, and skin malignancies. These risks are associated with the intensity and duration of immunosuppression.

Based on this information and the mechanism of action, there is a concern about a potential risk with the use of topical calcineurin inhibitors, including ELIDEL Cream. While a causal relationship has not been established, rare cases of skin malignancy and lymphoma have been reported in patients treated with topical calcineurin inhibitors, including ELIDEL Cream. Therefore:

- ELIDEL Cream should not be used in immunocompromised adults and children.
- If signs and symptoms of atopic dermatitis do not improve within 6 weeks, patients should be re-examined by their healthcare provider and their diagnosis be confirmed (see PRECAUTIONS).
- The safety of ELIDEL Cream has not been established beyond one year of non-continuous use.

(See CLINICAL PHARMACOLOGY, WARNINGS, boxed WARNING, PRECAUTIONS, INDICATIONS AND USAGE, and DOSAGE AND ADMINISTRATION.)

PRECAUTIONS

General

The use of ELIDEL Cream should be avoided on malignant or pre-malignant skin conditions. Malignant or pre-malignant skin conditions, such as cutaneous T-cell lymphoma (CTCL), can present as dermatitis.

ELIDEL Cream should not be used in patients with Netherton’s Syndrome or other skin diseases where there is the potential for increased systemic absorption of pimecrolimus . The safety of ELIDEL Cream has not been established in patients with generalized erythroderma.

The use of ELIDEL Cream may cause local symptoms such as skin burning (burning sensation, stinging, soreness) or pruritus. Localized symptoms are most common during the first few days of ELIDEL Cream application and typically improve as the lesions of atopic dermatitis resolve (see ADVERSE REACTIONS).

Bacterial and Viral Skin Infections: Before commencing treatment with ELIDEL Cream, bacterial or viral infections at treatment sites should be resolved. Studies have not evaluated the safety and efficacy of ELIDEL Cream in the treatment of clinically infected atopic dermatitis.

While patients with atopic dermatitis are predisposed to superficial skin infections including eczema herpeticum (Kaposi’s varicelliform eruption), treatment with ELIDEL Cream may be independently associated with an increased risk of varicella zoster virus infection (chicken pox or shingles), herpes simplex virus infection, or eczema herpeticum.

In clinical studies, 15/1,544 (1%) cases of skin papilloma (warts) were observed in patients using ELIDEL Cream. The youngest patient was age 2 and the oldest was age 12. In cases where there is worsening of skin papillomas or they do not respond to conventional therapy, discontinuation of ELIDEL Cream should be considered until complete resolution of the warts is achieved.

Patients with Lymphadenopathy: In clinical studies, 14/1,544 (0.9%) cases of lymphadenopathy were reported while using ELIDEL Cream. These cases of lymphadenopathy were usually related to infections and noted to resolve upon appropriate antibiotic therapy. Of these 14 cases, the majority had either a clear etiology or were known to resolve. Patients who receive ELIDEL Cream and who develop lymphadenopathy should have the etiology of their lymphadenopathy investigated. In the absence of a clear etiology for the lymphadenopathy, or in the presence of acute infectious mononucleosis, ELIDEL Cream should be discontinued. Patients who develop lymphadenopathy should be monitored to ensure that the lymphadenopathy resolves.

Sun Exposure: During the course of treatment, it is prudent for patients to minimize or avoid natural or artificial sunlight exposure, even while ELIDEL is not on the skin. The potential effects of ELIDEL Cream on skin response to ultraviolet damage are not known.

Immunocompromised Patients: The safety and efficacy of ELIDEL Cream in immunocompromised patients have not been studied.

Information for Patients

(See Medication Guide.)

Patients using ELIDEL Cream should receive the following information and instructions:

What is the most important information a patient should know about ELIDEL Cream?

The safety of using ELIDEL Cream for a long period of time is not known. A very small number of people who have used ELIDEL Cream have had cancer (for example, skin or lymphoma). However, a link with ELIDEL Cream use has not been shown. Because of this concern:

- A patient should not use ELIDEL Cream continuously for a long time.
- ELIDEL Cream should be used only on areas of skin that have eczema.
- ELIDEL Cream is not for use on a child under 2 years old.

How should a patient use ELIDEL Cream?

- A patient should use ELIDEL Cream exactly as prescribed.
- A patient should use ELIDEL Cream only on areas of skin that have eczema.
- A patient should use ELIDEL Cream for short periods, and if needed, treatment may be repeated with breaks in between.
- A patient should stop ELIDEL Cream when the signs and symptoms of eczema, such as itching, rash, and redness go away, or as directed by the physician.
- A patient should follow the physician’s advice if symptoms of eczema return after a treatment with ELIDEL Cream.
- A patient should contact the physician if:
  - symptoms get worse with ELIDEL Cream
  - the patient gets a skin infection
  - symptoms do not improve after 6 weeks of treatment

To apply ELIDEL Cream:

- A patient or caregiver should wash their hands before using ELIDEL Cream. When applying ELIDEL Cream after a bath or shower, the skin should be dry.
- A patient or caregiver should apply a thin layer of ELIDEL Cream only to the affected skin areas, twice a day, as directed by the physician.
- A patient or caregiver should use the smallest amount of ELIDEL Cream needed to control the signs and symptoms of eczema.
- Caregivers applying ELIDEL Cream to a patient, or a patient who is not treating the hands should wash their hands with soap and water after applying ELIDEL Cream. This should remove any cream left on the hands.
- A patient should not bathe, shower or swim right after applying ELIDEL Cream. This could wash off the cream.
- A patient can use moisturizers with ELIDEL Cream. They should be sure to check with the physician first about the products that are right for them. Because the skin of patients with eczema can be very dry, it is important they keep up good skin care practices. If a patient uses moisturizers, he or she should apply them after ELIDEL Cream.

What should a patient avoid while using ELIDEL Cream?

- A patient should not use sun lamps, tanning beds, or get treatment with ultraviolet light therapy during treatment with ELIDEL Cream.
- A patient should limit sun exposure during treatment with ELIDEL Cream even when the medicine is not on the skin. If a patient needs to be outdoors after applying ELIDEL Cream, the patient should wear loose fitting clothing that protects the treated area from the sun. The physician should advise the patient about other types of protection from the sun.
- A patient should not cover the skin being treated with bandages, dressings or wraps. A patient can wear normal clothing.
- A patient should not use ELIDEL Cream in the eyes. If ELIDEL Cream gets in the eyes, a patient should rinse them with cold water.
- A patient should not swallow ELIDEL Cream and should contact the physician if they do.

Drug Interactions

Potential interactions between ELIDEL and other drugs, including immunizations, have not been systematically evaluated. Due to low blood levels of pimecrolimus detected in some patients after topical application, systemic drug interactions are not expected, but cannot be ruled out. The concomitant administration of known CYP3A family of inhibitors in patients with widespread and/or erythrodermic disease should be done with caution. Some examples of such drugs are erythromycin, itraconazole, ketoconazole, fluconazole, calcium channel blockers and cimetidine.

Carcinogenesis, Mutagenesis, Impairment of Fertility

In a 2-year rat dermal carcinogenicity study using ELIDEL Cream, a statistically significant increase in the incidence of follicular cell adenoma of the thyroid was noted in low, mid and high dose male animals compared to vehicle and saline control male animals. Follicular cell adenoma of the thyroid was noted in the dermal rat carcinogenicity study at the lowest dose of 2 mg/kg/day [0.2% pimecrolimus cream; 1.5X the Maximum Recommended Human Dose (MRHD) based on AUC comparisons]. No increase in the incidence of follicular cell adenoma of the thyroid was noted in the oral carcinogenicity study in male rats up to 10 mg/kg/day (66X MRHD based on AUC comparisons). However, oral studies may not reflect continuous exposure or the same metabolic profile as by the dermal route. In a mouse dermal carcinogenicity study using pimecrolimus in an ethanolic solution, no increase in incidence of neoplasms was observed in the skin or other organs up to the highest dose of 4 mg/kg/day (0.32% pimecrolimus in ethanol) 27X MRHD based on AUC comparisons. However, lymphoproliferative changes (including lymphoma) were noted in a 13 week repeat dose dermal toxicity study conducted in mice using pimecrolimus in an ethanolic solution at a dose of 25 mg/kg/day (47X MRHD based on AUC comparisons). No lymphoproliferative changes were noted in this study at a dose of 10 mg/kg/day (17X MRHD based on AUC comparison). However, the latency time to lymphoma formation was shortened to 8 weeks after dermal administration of pimecrolimus dissolved in ethanol at a dose of 100 mg/kg/day (179-217X MRHD based on AUC comparisons).

In a mouse oral (gavage) carcinogenicity study, a statistically significant increase in the incidence of lymphoma was noted in high dose male and female animals compared to vehicle control male and female animals. Lymphomas were noted in the oral mouse carcinogenicity study at a dose of 45 mg/kg/day (258-340X MRHD based on AUC comparisons). No drug-related tumors were noted in the mouse oral carcinogenicity study at a dose of 15 mg/kg/day (60-133X MRHD based on AUC comparisons). In an oral (gavage) rat carcinogenicity study, a statistically significant increase in the incidence of benign thymoma was noted in 10 mg/kg/day pimecrolimus treated male and female animals compared to vehicle control treated male and female animals. In addition, a significant increase in the incidence of benign thymoma was noted in another oral (gavage) rat carcinogenicity study in 5 mg/kg/day pimecrolimus treated male animals compared to vehicle control treated male animals. No drug-related tumors were noted in the rat oral carcinogenicity study at a dose of 1 mg/kg/day male animals (1.1X MRHD based on AUC comparisons) and at a dose of 5 mg/kg/day for female animals (21X MRHD based on AUC comparisons).

In a 52-week dermal photo-carcinogenicity study, the median time to onset of skin tumor formation was decreased in hairless mice following chronic topical dosing with concurrent exposure to UV radiation (40 weeks of treatment followed by 12 weeks of observation) with the ELIDEL Cream vehicle alone. No additional effect on tumor development beyond the vehicle effect was noted with the addition of the active ingredient, pimecrolimus, to the vehicle cream.

A 39-week oral monkey toxicology study was conducted with pimecrolimus doses of 15, 45 and 120 mg/kg/day. A dose dependent increase in expression of immunosuppressive-related lymphoproliferative disorder (IRLD) associated with lymphocryptovirus (a monkey strain of virus related to human Epstein Barr virus) was observed. IRLD in monkeys mirrors what has been noted in human transplant patients after chronic systemic immunosuppressive therapy, post transplantation lymphoproliferative disease (PTLD), after treatment with chronic systemic immunosuppressive therapy. Both IRLD and PTLD can progress to lymphoma, which is dependent on the dose and duration of systemic immunosuppressive therapy. A dose dependent increase in opportunistic infections (a signal of systemic immunosuppression) was also noted in this monkey study. A no observed adverse effect level (NOAEL) for IRLD and opportunistic infections was not established in this study. IRLD occurred at the lowest dose of 15 mg/kg/day for 39 weeks [31X the Maximum Recommended Human Dose (MRHD) of ELIDEL Cream based on AUC comparisons] in this study. A partial recovery from IRLD was noted upon cessation of dosing in this study.

A battery of in vitro genotoxicity tests, including Ames assay, mouse lymphoma L5178Y assay, and chromosome aberration test in V79 Chinese hamster cells and an in vivo mouse micronucleus test revealed no evidence for a mutagenic or clastogenic potential for the drug.

An oral fertility and embryofetal developmental study in rats revealed estrus cycle disturbances, post-implantation loss and reduction in litter size at the 45 mg/kg/day dose (38X MRHD based on AUC comparisons). No effect on fertility in female rats was noted at 10 mg/kg/day (12X MRHD based on AUC comparisons). No effect on fertility in male rats was noted at 45 mg/kg/day (23X MRHD based on AUC comparisons), which was the highest dose tested in this study.

A second oral fertility and embryofetal developmental study in rats revealed reduced testicular and epididymal weights, reduced testicular sperm counts and motile sperm for males and estrus cycle disturbances, decreased corpora lutea, decreased implantations and viable fetuses for females at 45 mg/kg/day dose (123X MRHD for males and 192X MRHD for females based on AUC comparisons). No effect on fertility in female rats was noted at 10 mg/kg/day (5X MRHD based on AUC comparisons). No effect on fertility in male rats was noted at 2 mg/kg/day (0.7X MRHD based on AUC comparisons).

Pregnancy

Teratogenic Effects: Pregnancy Category C

There are no adequate and well-controlled studies of topically administered pimecrolimus in pregnant women. The experience with ELIDEL Cream when used by pregnant women is too limited to permit assessment of the safety of its use during pregnancy.

In dermal embryofetal developmental studies, no maternal or fetal toxicity was observed up to the highest practicable doses tested, 10 mg/kg/day (1% pimecrolimus cream) in rats (0.14X MRHD based on body surface area) and 10 mg/kg/day (1% pimecrolimus cream) in rabbits (0.65X MRHD based on AUC comparisons). The 1% pimecrolimus cream was administered topically for 6 hours/day during the period of organogenesis in rats and rabbits (gestational days 6-21 in rats and gestational days 6-20 in rabbits).

A second dermal embryofetal development study was conducted in rats using pimecrolimus cream applied dermally to pregnant rats (1 g cream/kg body weight of 0.2%, 0.6% and 1.0% pimecrolimus cream) from gestation day 6 to 17 at doses of 2, 6, and 10 mg/kg/day with daily exposure of approximately 22 hours. No maternal, reproductive, or embryo-fetal toxicity attributable to pimecrolimus was noted at 10 mg/kg/day (0.66X MRHD based on AUC comparisons), the highest dose evaluated in this study. No teratogenicity was noted in this study at any dose.

A combined oral fertility and embryofetal developmental study was conducted in rats and an oral embryofetal developmental study was conducted in rabbits. Pimecrolimus was administered during the period of organogenesis (2 weeks prior to mating until gestational day 16 in rats, gestational days 6-18 in rabbits) up to dose levels of 45 mg/kg/day in rats and 20 mg/kg/day in rabbits. In the absence of maternal toxicity, indicators of embryofetal toxicity (post-implantation loss and reduction in litter size) were noted at 45 mg/kg/day (38X MRHD based on AUC comparisons) in the oral fertility and embryofetal developmental study conducted in rats. No malformations in the fetuses were noted at 45 mg/kg/day (38X MRHD based on AUC comparisons) in this study. No maternal toxicity, embryotoxicity or teratogenicity were noted in the oral rabbit embryofetal developmental toxicity study at 20 mg/kg/day (3.9X MRHD based on AUC comparisons), which was the highest dose tested in this study.

A second oral embryofetal development study was conducted in rats. Pimecrolimus was administered during the period of organogenesis (gestational days 6 – 17) at doses of 2, 10 and 45 mg/kg/day. Maternal toxicity, embryolethality and fetotoxicity were noted at 45 mg/kg/day (271X MRHD based on AUC comparisons). A slight increase in skeletal variations that were indicative of delayed skeletal ossification was also noted at this dose. No maternal toxicity, embryolethality or fetotoxicity were noted at 10 mg/kg/day (16X MRHD based on AUC comparisons). No teratogenicity was noted in this study at any dose.

A second oral embryofetal development study was conducted in rabbits. Pimecrolimus was administered during the period of organogenesis (gestational days 7 – 20) at doses of 2, 6 and 20 mg/kg/day. Maternal toxicity, embryotoxicity and fetotoxicity were noted at 20 mg/kg/day (12X MRHD based on AUC comparisons). A slight increase in skeletal variations that were indicative of delayed skeletal ossification was also noted at this dose. No maternal toxicity, embryotoxicity or fetotoxicity were noted at 6 mg/kg/day (5X MRHD based on AUC comparisons). No teratogenicity was noted in this study at any dose.

An oral peri- and post-natal developmental study was conducted in rats. Pimecrolimus was administered from gestational day 6 through lactational day 21 up to a dose level of 40 mg/kg/day. Only 2 of 22 females delivered live pups at the highest dose of 40 mg/kg/day. Postnatal survival, development of the F1 generation, their subsequent maturation and fertility were not affected at 10 mg/kg/day (12X MRHD based on AUC comparisons), the highest dose evaluated in this study.

Pimecrolimus was transferred across the placenta in oral rat and rabbit embryofetal developmental studies.

There are, however, no adequate and well-controlled studies in pregnant women. Because animal reproduction studies are not always predictive of human response, this drug should be used only if clearly needed during pregnancy.

Nursing Mothers

It is not known whether this drug is excreted in human milk. Because of the potential for serious adverse reactions in nursing infants from pimecrolimus, a decision should be made whether to discontinue nursing or to discontinue the drug, taking into account the importance of the drug to the mother.

Pediatric Use

ELIDEL Cream is not indicated for use in children less than 2 years of age.

The long-term safety and effects of ELIDEL Cream on the developing immune system are unknown (see WARNINGS, boxed WARNING, and INDICATIONS AND USAGE).

Three Phase 3 pediatric studies were conducted involving 1,114 patients 2-17 years of age. Two studies were 6-week randomized vehicle-controlled studies with a 20-week open-label phase and one was a vehicle-controlled (up to 1 year) safety study with the option for sequential topical corticosteroid use. Of these patients 542 (49%) were 2-6 years of age. In the short-term studies, 11% of ELIDEL patients did not complete these studies and 1.5% of ELIDEL patients discontinued due to adverse events. In the one-year study, 32% of ELIDEL patients did not complete this study and 3% of ELIDEL patients discontinued due to adverse events. Most discontinuations were due to unsatisfactory therapeutic effect.

The most common local adverse event in the short-term studies of ELIDEL Cream in pediatric patients ages 2-17 was application site burning (10% vs. 13% vehicle); the incidence in the long-term study was 9% ELIDEL vs. 7% vehicle (see ADVERSE REACTIONS). Adverse events that were more frequent (>5%) in patients treated with ELIDEL Cream compared to vehicle were headache (14% vs. 9%) in the short-term trial. Nasopharyngitis (26% vs. 21%), influenza (13% vs. 4%), pharyngitis (8% vs. 3%), viral infection (7% vs. 1%), pyrexia (13% vs. 5%), cough (16% vs. 11%), and headache (25% vs. 16%) were increased over vehicle in the 1-year safety study (see ADVERSE REACTIONS). In 843 patients ages 2-17 years treated with ELIDEL Cream, 9 (0.8%) developed eczema herpeticum (5 on ELIDEL Cream alone and 4 on ELIDEL Cream used in sequence with corticosteroids). In 211 patients on vehicle alone, there were no cases of eczema herpeticum. The majority of adverse events were mild to moderate in severity.

Two Phase 3 studies were conducted involving 436 infants age 3 months-23 months. One 6-week randomized vehicle-controlled study with a 20-week open-label phase and one safety study, up to one year, were conducted. In the 6-week study, 11% of ELIDEL and 48% of vehicle patients did not complete this study; no patient in either group discontinued due to adverse events. Infants on ELIDEL Cream had an increased incidence of some adverse events compared to vehicle. In the 6-week vehicle-controlled study these adverse events included pyrexia (32% vs. 13% vehicle), URI (24% vs. 14%), nasopharyngitis (15% vs. 8%), gastroenteritis (7% vs. 3%), otitis media (4% vs. 0%), and diarrhea (8% vs. 0%). In the open-label phase of the study, for infants who switched to ELIDEL Cream from vehicle, the incidence of the above-cited adverse events approached or equaled the incidence of those patients who remained on ELIDEL Cream. In the 6 month safety data, 16% of ELIDEL and 35% of vehicle patients discontinued early and 1.5% of ELIDEL and 0% of vehicle patients discontinued due to adverse events. Infants on ELIDEL Cream had a greater incidence of some adverse events as compared to vehicle. These included pyrexia (30% vs. 20%), URI (21% vs. 17%), cough (15% vs. 9%), hypersensitivity (8% vs. 2%), teething (27% vs. 22%), vomiting (9% vs. 4%), rhinitis (13% vs. 9%), viral rash (4% vs. 0%), rhinorrhea (4% vs. 0%), and wheezing (4% vs. 0%).

Geriatric Use

Nine (9) patients ≥65 years old received ELIDEL Cream in Phase 3 studies. Clinical studies of ELIDEL did not include sufficient numbers of patients aged 65 and over to assess efficacy and safety.

ADVERSE REACTIONS

No phototoxicity and no photoallergenicity were detected in clinical studies with 24 and 33 normal volunteers, respectively. In human dermal safety studies, ELIDEL ® (pimecrolimus) Cream 1% did not induce contact sensitization or cumulative irritation.

In a one-year safety study in pediatric patients age 2-17 years old involving sequential use of ELIDEL Cream and a topical corticosteroid, 43% of ELIDEL patients and 68% of vehicle patients used corticosteroids during the study. Corticosteroids were used for more than 7 days by 34% of ELIDEL patients and 54% of vehicle patients. An increased incidence of impetigo, skin infection, superinfection (infected atopic dermatitis), rhinitis, and urticaria were found in the patients that had used ELIDEL Cream and topical corticosteroid sequentially as compared to ELIDEL Cream alone.

In 3 randomized, double-blind vehicle-controlled pediatric studies and one active-controlled adult study, 843 and 328 patients respectively, were treated with ELIDEL Cream. In these clinical trials, 48 (4%) of the 1,171 ELIDEL patients and 13 (3%) of 408 vehicle-treated patients discontinued therapy due to adverse events. Discontinuations for AEs were primarily due to application site reactions, and cutaneous infections. The most common application site reaction was application site burning, which occurred in 8%-26% of patients treated with ELIDEL Cream.

The following table depicts the incidence of adverse events pooled across the 2 identically designed 6-week studies with their open label extensions and the 1-year safety study for pediatric patients ages 2-17. Data from the adult active-controlled study is also included in this table. Adverse events are listed regardless of relationship to study drug.

Treatment Emergent Adverse Events (≥ 1%) in Elidel® Treatment Groups
 | Pediatric Patients*Vehicle-Controlled(6 weeks) |  | Pediatric Patients* Open-Label (20 weeks) |  | Pediatric Patients* Vehicle-Controlled(1 year) |  | Adult Active Comparator (1 year)
 | Elidel® Cream (N=267) N (%) | Vehicle(N=136) N (%) | Elidel® Cream (N=335) N (%) |  | Elidel® Cream (N=272) N (%) | Vehicle(N=75) N (%) | Elidel® Cream(N=328)N (%)
At least 1 AE | 182 (68.2%) | 97 (71.3%) | 240 (72.0%) |  | 230 (84.6%) | 56 (74.7%) | 256 (78.0%)
Infections and Infestations
Upper Respiratory Tract Infection NOS | 38 (14.2%) | 18 (13.2%) | 65 (19.4%) |  | 13 (4.8%) | 6 (8.0%) | 14 (4.3%)
Nasopharyngitis | 27 (10.1%) | 10 (7.4%) | 32 (19.6%) |  | 72 (26.5%) | 16 (21.3%) | 25 (7.6%)
Skin Infection NOS | 8 (3.0%) | 9 (5.1%) | 18 (5.4%) |  | 6 (2.2%) | 3 (4.0%) | 21 (6.4%)
Influenza | 8 (3.0%) | 1 (0.7%) | 22 (6.6%) |  | 36 (13.2%) | 3 (4.0%) | 32 (9.8%)
Ear Infection NOS | 6 (2.2%) | 2 (1.5%) | 19 (5.7%) |  | 9 (3.3%) | 1 (1.3%) | 2 (0.6%)
Otitis Media | 6 (2.2%) | 1 (0.7%) | 10 (3.0%) |  | 8 (2.9%) | 4 (5.3%) | 2 (0.6%)
Impetigo | 5 (1.9%) | 3 (2.2%) | 12 (3.6%) |  | 11 (4.0%) | 4 (5.3%) | 8 (2.4%)
Bacterial Infection | 4 (1.5%) | 3 (2.2%) | 4 (1.2%) |  | 3 (1.1%) | 0 | 6 (1.8%)
Folliculitis | 3 (1.1%) | 1 (0.7%) | 3 (0.9%) |  | 6 (2.2%) | 3 (4.0%) | 20 (6.1%)
Sinusitis | 3 (1.1%) | 1 (0.7%) | 11 (3.3%) |  | 6 (2.2%) | 1 (1.3%) | 2 (0.6%)
Pneumonia NOS | 3 (1.1%) | 1 (0.7%) | 5 (1.5%) |  | 0 | 1 (1.3%) | 1 (0.3%)
Pharyngitis NOS | 2 (0.7%) | 2 (1.5%) | 3 (0.9%) |  | 22 (8.1%) | 2 (2.7%) | 3 (0.9%)
Pharyngitis Streptococcal | 2 (0.7%) | 2 (1.5%) | 10 (3.0%) |  | 0 | <1% | 0
Molluscum Contagiosum | 2 (0.7%) | 0 | 4 (1.2%) |  | 5 (1.8%) | 0 | 0
Staphylococcal Infection | 1 (0.4%) | 5 (3.7%) | 7 (2.1%) |  | 0 | <1% | 3 (0.9%)
Bronchitis NOS | 1 (0.4%) | 3 (2.2%) | 4 (1.2%) |  | 29 (10.7%) | 6 (8.0%) | 8 (2.4%)
Herpes Simplex | 1 (0.4%) | 0 | 4 (1.2%) |  | 9 (3.3%) | 2 (2.7%) | 13 (4.0%)
Tonsillitis NOS | 1 (0.4%) | 0 | 3 (0.9%) |  | 17 (6.3%) | 0 | 2 (0.6%)
Viral Infection NOS | 2 (0.7%) | 1 (0.7%) | 1 (0.3%) |  | 18 (6.6%) | 1 (1.3%) | 0
Gastroenteritis NOS | 0 | 3 (2.2%) | 2 (0.6%) |  | 20 (7.4%) | 2 (2.7%) | 6 (1.8%)
Chickenpox | 2 (0.7%) | 0 | 3 (0.9%) |  | 8 (2.9%) | 3 (4.0%) | 1 (0.3%)
Skin Papilloma | 1 (0.4%) | 0 | 2 (0.6%) |  | 9 (3.3%) | <1% | 0
Tonsillitis Acute NOS | 0 | 0 | 0 |  | 7 (2.6%) | 0 | 0
Upper Respiratory Tract Infection Viral NOS | 1 (0.4%) | 0 | 3 (0.9%) |  | 4 (1.5%) | 0 | 1 (0.3%)
Herpes Simplex Dermatitis | 0 | 0 | 1 (0.3%) |  | 4 (1.5%) | 0 | 2 (0.6%)
Bronchitis Acute NOS | 0 | 0 | 0 |  | 4 (1.5%) | 0 | 0
Eye Infection NOS | 0 | 0 | 0 |  | 3 (1.1%) | <1% | 1 (0.3%)
General Disorders and Administration Site Conditions
Application Site Burning | 28 (10.4%) | 17 (12.5%) | 5 (1.5%) |  | 23 (8.5%) | 5 (6.7%) | 85 (25.9%)
Pyrexia | 20 (7.5%) | 12 (8.8%) | 41 (12.2%) |  | 34 (12.5%) | 4 (5.3%) | 4 (1.2%)
Application Site Reaction NOS | 8 (3.0%) | 7 (5.1%) | 7 (2.1%) |  | 9 (3.3%) | 2 (2.7%) | 48 (14.6%)
Application Site Irritation | 8 (3.0%) | 8 (5.9%) | 3 (0.9%) |  | 1 (0.4%) | 3 (4.0%) | 21 (6.4%)
Influenza Like Illness | 1 (0.4%) | 0 | 2 (0.6%) |  | 5 (1.8%) | 2 (2.7%) | 6 (1.8%)
Application Site Erythema | 1 (0.4%) | 0 | 0 |  | 6 (2.2%) | 0 | 7 (2.1%)
Application Site Pruritus | 3 (1.1%) | 2 (1.5%) | 2 (0.6%) |  | 5 (1.8%) | 0 | 18 (5.5%)
Respiratory, Thoracic and Mediastinal Disorders
Cough | 31 (11.6%) | 11 (8.1%) | 31 (9.3%) |  | 43 (15.8%) | 8 (10.7%) | 8 (2.4%)
Nasal Congestion | 7 (2.6%) | 2 (1.5%) | 6 (1.8%) |  | 4 (1.5%) | 1 (1.3%) | 2 (0.6%)
Rhinorrhea | 5 (1.9%) | 1 (0.7%) | 3 (0.9%) |  | 1 (0.4%) | 1 (1.3%) | 0
Asthma Aggravated | 4 (1.5%) | 3 (2.2%) | 13 (3.9%) |  | 3 (1.1%) | 1 (1.3%) | 0
Sinus Congestion | 3 (1.1%) | 1 (0.7%) | 2 (0.6%) |  | <1% | <1% | 3 (0.9%)
Rhinitis | 1 (0.4%) | 0 | 5 (1.5%) |  | 12 (4.4%) | 5 (6.7%) | 7 (2.1%)
Wheezing | 1 (0.4%) | 1 (0.7%) | 4 (1.2%) |  | 2 (0.7%) | <1% | 0
Asthma NOS | 2 (0.7%) | 1 (0.7%) | 11 (3.3%) |  | 10 (3.7%) | 2 (2.7%) | 8 (2.4%)
Epistaxis | 0 | 1 (0.7%) | 0 |  | 9 (3.3%) | 1 (1.3%) | 1 (0.3%)
Dyspnea NOS | 0 | 0 | 0 |  | 5 (1.8%) | 1 (1.3%) | 2 (0.6%)
Gastrointestinal Disorders
Abdominal Pain Upper | 11 (4.1%) | 6 (4.4%) | 10 (3.0%) |  | 15 (5.5%) | 5 (6.7%) | 1 (0.3%)
Sore Throat | 9 (3.4%) | 5 (3.7%) | 15 (5.4%) |  | 22 (8.1%) | 4 (5.3%) | 12 (3.7%)
Vomiting NOS | 8 (3.0%) | 6 (4.4%) | 14 (4.2%) |  | 18 (6.6%) | 6 (8.0%) | 2 (0.6%)
Diarrhea NOS | 3 (1.1%) | 1 (0.7%) | 2 (0.6%) |  | 21 (7.7%) | 4 (5.3%) | 7 (2.1%)
Nausea | 1 (0.4%) | 3 (2.2%) | 4 (1.2%) |  | 11 (4.0%) | 5 (6.7%) | 6 (1.8%)
Abdominal Pain NOS | 1 (0.4%) | 1 (0.7%) | 5 (1.5%) |  | 12 (4.4%) | 3 (4.0%) | 1 (0.3%)
Toothache | 1 (0.4%) | 1 (0.7%) | 2 (0.6%) |  | 7 (2.6%) | 1 (1.3%) | 2 (0.6%)
Constipation | 1 (0.4%) | 0 | 2 (0.6%) |  | 10 (3.7%) | <1% | 0
Loose Stools | 0 | 1 (0.7%) | 4 (1.2%) |  | <1% | <1% | 0
Reproductive System and Breast Disorders
Dysmenorrhea | 3 (1.1%) | 0 | 5 (1.5%) |  | 3 (1.1%) | 1 (1.3%) | 4 (1.2%)
Eye Disorders
Conjunctivitis NEC | 2 (0.7%) | 1 (0.7%) | 7 (2.1%) |  | 6 (2.2%) | 3 (4.0%) | 10 (3.0%)
Skin & Subcutaneous Tissue Disorders
Urticaria | 3 (1.1%) | 0 | 1 (0.3%) |  | 1 (0.4%) | <1% | 3 (0.9%)
Acne NOS | 0 | 1 (0.7%) | 1 (0.3%) |  | 4 (1.5%) | <1% | 6 (1.8%)
Immune System Disorders
Hypersensitivity NOS | 11 (4.1%) | 6 (4.4%) | 16 (4.8%) |  | 14 (5.1%) | 1 (1.3%) | 11 (3.4%)
Injury and Poisoning
Accident NOS | 3 (1.1%) | 1 (0.7%) | 1 (0.3%) |  | <1% | 1 (1.3%) | 0
Laceration | 2 (0.7%) | 1 (0.7%) | 5 (1.5%) |  | <1% | <1% | 0
Musculoskeletal, Connective Tissue and Bone Disorders
Back Pain | 1 (0.4%) | 2 (1.5%) | 1 (0.3%) |  | <1% | 0 | 6 (1.8%)
Arthralgias | 0 | 0 | 1 (0.3%) |  | 3 (1.1%) | 1 (1.3%) | 5 (1.5%)
Ear and Labyrinth Disorders
Earache | 2 (0.7%) | 1 (0.7%) | 0 |  | 8 (2.9%) | 2 (2.7%) | 0
Nervous System Disorders
Headache | 37 (13.9%) | 12 (8.8%) | 38 (11.3%) |  | 69 (25.4%) | 12 (16.0%) | 23 (7.0%)

*Ages 2-17 years

Two cases of septic arthritis have been reported in infants less than one year of age in clinical trials conducted with ELIDEL Cream (n = 2,443). Causality has not been established.

POST-MARKETING EVENTS

The following adverse reactions have been reported in patients using ELIDEL Cream. Because these reactions are reported voluntarily from a population of uncertain size, it is not always possible to reliably estimate their frequency or establish a causal relationship to drug exposure.

General: Anaphylactic reactions, ocular irritation after application of the cream to the eye lids or near the eyes, angioneurotic edema, facial edema, skin flushing associated with alcohol use, skin discoloration

Hematology/Oncology: Lymphomas, basal cell carcinoma, malignant melanoma, squamous cell carcinoma

OVERDOSAGE

There has been no experience of overdose with ELIDEL ® (pimecrolimus) Cream 1%. If oral ingestion occurs, medical advice should be sought.

DOSAGE AND ADMINISTRATION

- The patient or care giver should apply a thin layer of ELIDEL (pimecrolimus) Cream 1% to the affected skin twice daily. The patient or caregiver should stop using when signs and symptoms (e.g., itch, rash and redness) resolve and should be instructed on what actions to take if symptoms recur.
- If signs and symptoms persist beyond 6 weeks, patients should be re-examined by their health care provider to confirm the diagnosis of atopic dermatitis.
- Continuous long-term use of ELIDEL Cream should be avoided, and application should be limited to areas of involvement with atopic dermatitis.

The safety of ELIDEL Cream under occlusion, which may promote systemic exposure, has not been evaluated. ELIDEL Cream should not be used with occlusive dressings.

HOW SUPPLIED

ELIDEL ® (pimecrolimus) Cream 1% is available in tubes of 30 grams, 60 grams, and 100 grams.

30 gram tube.................................................................................................NDC 54868-4878-0

60 gram tube……………………………………………………………….NDC 54868-4878-2

100 gram tube……………………………………………………………...NDC 54868-4878-1

Store at 25°C (77°F); excursions permitted to 15°C-30°C (59°F-86°F). Do not freeze.

Manufactured by:

Novartis Pharma Produktions GmbH

Wehr, Germany

Distributed by:

Novartis Pharmaceuticals Corp.

East Hanover, NJ 07936

Relabeling of "Additional Barcode Label" by:
Physicians Total Care, Inc.

Tulsa, OK 74146

MEDICATION GUIDE

ELIDEL® [EĹ-ee-del] (pimecrolimus) Cream 1%

You must read and follow all instructions before using ELIDEL Cream.

Read the Medication Guide you get every time you or a family member gets ELIDEL Cream. There may be new information. This Medication Guide does not take the place of talking with your doctor about your medical condition or treatment. If you have any questions about ELIDEL Cream, ask your doctor or pharmacist.

What is the most important information I should know about ELIDEL Cream?

The safety of using ELIDEL Cream for a long period of time is not known. A very small number of people who have used ELIDEL Cream have had cancer (for example, skin or lymphoma). However, a link with ELIDEL Cream use has not been shown. Because of this concern:

- Do not use ELIDEL Cream continuously for a long time.
- Use ELIDEL Cream only on areas of your skin that have eczema.
- Do not use ELIDEL Cream on a child under 2 years old.

What is ELIDEL Cream?

ELIDEL Cream is a prescription medicine used on the skin (topical) to treat eczema (atopic dermatitis). ELIDEL Cream is in a class of medicines called topical calcineurin inhibitors. ELIDEL Cream is for adults and children age 2 years and older who do not have a weakened immune system. ELIDEL Cream is used on the skin for short periods, and if needed, treatment may be repeated with breaks in between. ELIDEL Cream is for use after other prescription medicines have not worked for you or if your doctor recommends that other prescription medicines should not be used.

Who should not use ELIDEL Cream?

Do not use ELIDEL Cream:

- on children under 2 years of age
- if you are allergic to ELIDEL Cream or anything in it. See the end of this Medication Guide for a complete list of ingredients.

What should I tell my doctor before starting ELIDEL Cream?

Before you start using ELIDEL Cream, tell your doctor about all of your medical conditions, including if you:

- have a skin disease called Netherton’s syndrome (a rare inherited condition)
- have any infection on your skin including chicken pox or herpes
- have been told you have a weakened immune system
- are pregnant, breastfeeding, or planning to become pregnant.

Tell your doctor about all the medicines you take including prescription and nonprescription medicines, vitamins, and herbal supplements. Tell your doctor about all the skin medicines and products you use.

Know the medicines you take. Keep a list of them with you to show your doctor and pharmacist each time you get a new medicine.

How should I use ELIDEL Cream?

- Use ELIDEL Cream exactly as prescribed.
- Use ELIDEL Cream only on areas of your skin that have eczema.
- Use ELIDEL Cream for short periods, and if needed, treatment may be repeated with breaks in between.
- Stop ELIDEL Cream when the signs and symptoms of eczema, such as itching, rash, and redness go away, or as directed by your doctor.
- Follow your doctor’s advice if symptoms of eczema return after a treatment with ELIDEL Cream.
- Call your doctor if:
  - your symptoms get worse with ELIDEL Cream
  - you get an infection on your skin
  - your symptoms do not improve after 6 weeks of treatment. Sometimes other skin diseases can look like eczema.

To apply ELIDEL Cream:

- Wash your hands before using ELIDEL Cream. When applying ELIDEL Cream after a bath or shower, make sure your skin is dry.
- Apply a thin layer of ELIDEL Cream only to the affected skin areas, twice a day, as directed by your doctor.
- Use the smallest amount of ELIDEL Cream needed to control the signs and symptoms of eczema.
- If you are a caregiver applying ELIDEL Cream to a patient, or if you are a patient who is not treating your hands, wash your hands with soap and water after applying ELIDEL Cream. This should remove any cream left on the hands.
- Do not bathe, shower or swim right after applying ELIDEL Cream. This could wash off the cream.
- You can use moisturizers with ELIDEL Cream. Make sure you check with your doctor first about the products that are right for you. Because the skin of patients with eczema can be very dry, it is important to keep up good skin care practices. If you use moisturizers, apply them after ELIDEL Cream.

What should I avoid while using ELIDEL Cream?

- Do not use sun lamps, tanning beds, or get treatment with ultraviolet light therapy during treatment with ELIDEL Cream.
- Limit sun exposure during treatment with ELIDEL Cream even when the medicine is not on your skin. If you need to be outdoors after applying ELIDEL Cream, wear loose fitting clothing that protects the treated area from the sun. Ask your doctor what other types of protection from the sun you should use.
- Do not cover the skin being treated with bandages, dressings or wraps. You can wear normal clothing.
- Do not use ELIDEL Cream in the eyes. If ELIDEL Cream gets in your eyes rinse your eyes with cold water.
- Do not swallow ELIDEL Cream. If you do, call your doctor.

What are the possible side effects of ELIDEL Cream?

The most common side effect at the skin application site is burning or a feeling of warmth. These side effects are usually mild or moderate, happen during the first 5 days of treatment, and usually clear up in a few days. Call your doctor if the burning feeling is severe or lasts for more than 1 week.

Other side effects include headache, common cold or stuffy nose, sore throat, influenza, fever, viral infection, and cough. Some people may get viral skin infections (like cold sores, chicken pox, shingles, or warts) or swollen lymph nodes (glands).

Talk to your doctor if you have a skin infection or if side effects (for example, swollen glands) continue or bother you.

These are not all the side effects with ELIDEL Cream. Ask your doctor or pharmacist for more information.

How should I store ELIDEL Cream?

- Store ELIDEL Cream at room temperature between 59° to 86°F (15° to 30°C).
- Keep ELIDEL Cream and all medicines out of the reach of children.

General advice about ELIDEL Cream

Medicines are sometimes prescribed for purposes other than those listed in a Medication Guide. Use ELIDEL Cream only for the condition for which it was prescribed. Do not give ELIDEL Cream to other people even if they have the same symptoms you have, as it may not be right for them.

This Medication Guide summarizes the most important information about ELIDEL Cream. If you would like more information, talk with your doctor.

Your doctor or pharmacist can give you information about ELIDEL Cream that is written for health care professionals. For more information, you can also visit the Novartis Internet site at www.elidel.com or call the ELIDEL Cream help line at 877-4 ELIDEL (877-435-4335).

What are the ingredients in ELIDEL Cream?

Active ingredient:pimecrolimus

Inactive ingredients:benzyl alcohol, cetyl alcohol, citric acid, mono- and di-glycerides, oleyl alcohol, propylene glycol, sodium cetostearyl sulphate, sodium hydroxide, stearyl alcohol, triglycerides, and water.

Call your doctor for medical advice about side effects. You may report side effects to FDA at 1-800-FDA-1088

Manufactured by:

Novartis Pharma Produktions GmbH

Wehr, Germany

Distributed by:

Novartis Pharmaceuticals Corp.

East Hanover, New Jersey 07936

This Medication Guide has been approved by the U.S. Food and Drug Administration

MAY 2009 T2009-66/T2009-67

© Novartis

PRINCIPAL DISPLAY PANEL

Package Label

ELIDEL® (pimecrolimus) cream 1%

FOR DERMATOLOGIC USE ONLY. NOT FOR OPHTHALMIC USE.

Each gram contains 10 mg of pimecrolimus